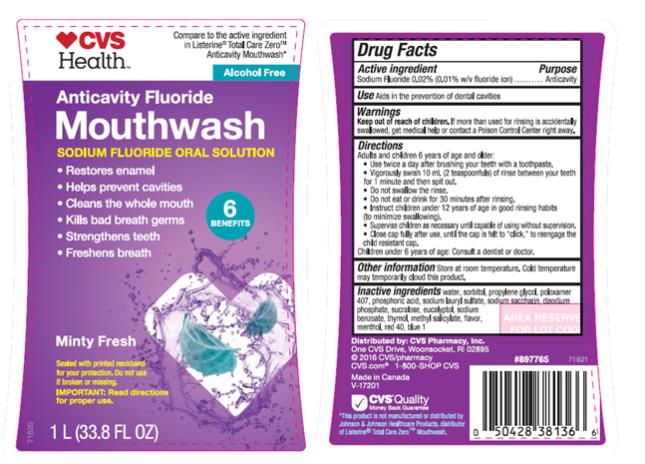 DRUG LABEL: Anticavity Fluoride
NDC: 69842-232 | Form: MOUTHWASH
Manufacturer: CVS Pharmacy
Category: otc | Type: HUMAN OTC DRUG LABEL
Date: 20170201

ACTIVE INGREDIENTS: SODIUM FLUORIDE 0.1 mg/1 mL
INACTIVE INGREDIENTS: WATER; SORBITOL; PROPYLENE GLYCOL; POLOXAMER 407; PHOSPHORIC ACID; SODIUM LAURYL SULFATE; SACCHARIN SODIUM; SODIUM PHOSPHATE, DIBASIC, ANHYDROUS; SUCRALOSE; EUCALYPTOL; SODIUM BENZOATE; THYMOL; METHYL SALICYLATE; MENTHOL; FD&C RED NO. 40; FD&C BLUE NO. 1

Anticavity Fluoride Mouthwash Minty Fresh

Drug Facts

Active ingredient

Sodium Fluoride 0.02% (0.01% w/v fluoride ion)

Purpose

Anticavity

Use

Aids in the prevention of dental cavities

Warnings

Keep out of reach of children.

If more than used for rinsing is accidentally swallowed, get medical help or contact a Poison Control Center right away.

Directions

Adults and children 6 years of age and older:

Use twice a day after brushing your teeth with a toothpaste.

Vigorously swish 10 mL (2 teaspoonfuls) of rinse between your teeth for 1 minute and then spit out.

Do not swallow the rinse.

Do not eat or drink for 30 minutes after rinsing.

Instruct children 12 years of age in good rinsing habits (to minimize swallowing).

Supervise children as necessary until capable of using without supervision.

Close cap fully after use, until the cap is felt to “click”, to reengage the child resistant cap.

Children under 6 years of age: Consult a dentist or doctor

Other information Store at room temperature. Cold temperature may temporarily cloud this product.

Inactive ingredients

water, sorbitol, propylene glycol, poloxamer 407, phosphoric acid, sodium lauryl sulfate, sodium saccharin, disodium phosphate, sucralose, eucalyptol, sodium benzoate, thymol, methyl salicylate, flavor, menthol, red 40, blue 1.

This rinse may cause temporary staining to the surface of teeth.

This is not harmful and adequate brushing may prevent its occurrence.

PRINCIPAL DISPLAY PANEL

Anticavity Fluoride
Mouthwash
Sodium Fluoride Oral Solution
Minty Fresh
1 L (33.8 FL OZ)